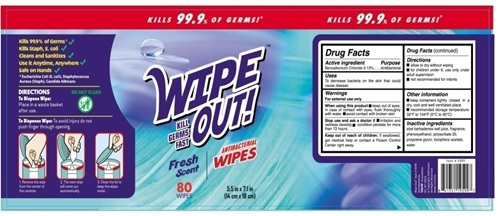 DRUG LABEL: WIPE OUT Antibacterial Wipes Fresh Scent
NDC: 80404-301 | Form: CLOTH
Manufacturer: Xinsanyang Pharmaceutical (Xiamen) Co., Ltd.
Category: otc | Type: HUMAN OTC DRUG LABEL
Date: 20201125

ACTIVE INGREDIENTS: BENZALKONIUM CHLORIDE 0.13 1/100 1
INACTIVE INGREDIENTS: PHENOXYETHANOL; POLYSORBATE 20; PROPYLENE GLYCOL; .ALPHA.-TOCOPHEROL ACETATE; WATER; FRAGRANCE LAVENDER & CHIA F-153480; ALOE VERA LEAF

WIPE OUT Antibacterial Wipes Fresh Scent

WIPE OUT Antibacterial Wipes Fresh Scent

ACTIVE INGREDIENT

Benzalkonium Chloride 0.13%

Purpose: Antiseptic

PURPOSE

Antiseptic, WIPE OUT Antibacterial Wipes Fresh Scent

INDICATIONS AND USAGE

WIPE OUT Antibacterial Wipes Fresh Scent to help reduce bacteria that potentially can cause disease. For use when soap and water are not available.

WARNINGS

For external use only. Flammable. Keep away from heat or flame

DO NOT USE

in children less than 2 months of age
on open skin wounds

When using this product keep out of eyes, ears, and mouth. In case of contact with eyes, rinse eyes thoroughly with water.
Stop use and ask a doctor if irritation or rash occurs. These may be signs of a serious condition.
Keep out of reach of children. If swallowed, get medical help or contact a Poison Control Center right away

Stop use and ask a doctor if irritation or rash occurs. These may be signs of a serious condition.

Keep out of reach of children. If swallowed, get medical help or contact a Poison Control Center right away.

DOSAGE AND ADMINISTRATION

Wipe the surface of the skin and let it dry naturally.
Supervise children under 6 years of age when using this product to avoid swallowing.

STORAGE AND HANDLING

Store between 15-30C (59-86F)
Avoid freezing and excessive heat above 40C (104F)

INACTIVE INGREDIENT

Aloe Barbadensis Leaf Juice
Fragrance
Phenoxyethanol
Polysorbate 20
Propylene Glycol
Tocopheryl Acetata
Water